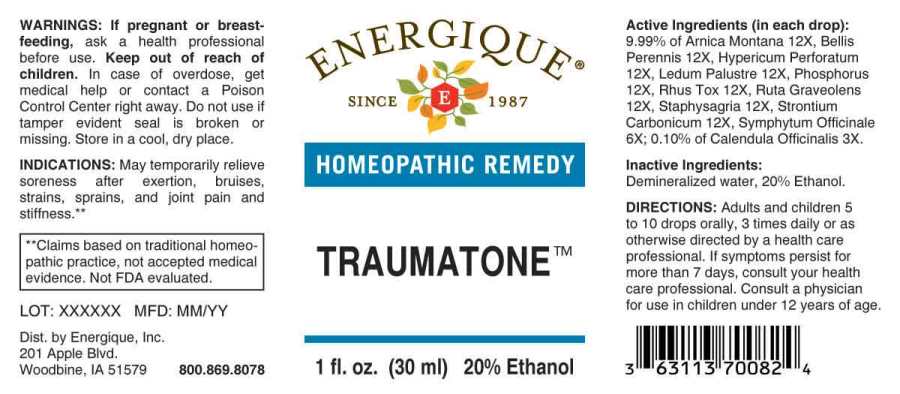 DRUG LABEL: Traumatone
NDC: 44911-0416 | Form: LIQUID
Manufacturer: Energique, Inc.
Category: homeopathic | Type: HUMAN OTC DRUG LABEL
Date: 20240801

ACTIVE INGREDIENTS: CALENDULA OFFICINALIS FLOWERING TOP 3 [hp_X]/1 mL; COMFREY ROOT 6 [hp_X]/1 mL; ARNICA MONTANA WHOLE 12 [hp_X]/1 mL; BELLIS PERENNIS WHOLE 12 [hp_X]/1 mL; HYPERICUM PERFORATUM WHOLE 12 [hp_X]/1 mL; RHODODENDRON TOMENTOSUM LEAFY TWIG 12 [hp_X]/1 mL; PHOSPHORUS 12 [hp_X]/1 mL; TOXICODENDRON PUBESCENS LEAF 12 [hp_X]/1 mL; RUTA GRAVEOLENS FLOWERING TOP 12 [hp_X]/1 mL; DELPHINIUM STAPHISAGRIA SEED 12 [hp_X]/1 mL; STRONTIUM CARBONATE 12 [hp_X]/1 mL
INACTIVE INGREDIENTS: WATER; ALCOHOL

Drug Facts:

ACTIVE INGREDIENTS:

(in each drop): 9.99% of Arnica Montana 12X, Bellis Perennis 12X, Hypericum Perforatum 12X, Ledum Palustre 12X, Phosphorus 12X, Rhus Tox 12X, Ruta Graveolens 12X, Staphysagria 12X, Strontium Carbonicum 12X, Symphytum Officinale 6X; 0.10% of Calendula Officinalis 3X.

INDICATIONS:

May temporarily relieve soreness after exertion, bruises, strains, sprains, and joint pain and stiffness.**

**Claims based on traditional homeopathic practice, not accepted medical evidence. Not FDA evaluated.

WARNINGS:

If pregnant or breastfeeding, ask a health professional before use.

Keep out of reach of children. In case of overdose, get medical help or contact a Poison Control Center right away.

Do not use if tamper evident seal is broken or missing.

Store in a cool, dry place.

Keep out of reach of children. In case of overdose, get medical help or contact a Poison Control Center right away.

DIRECTIONS:

Adults and children 5 to 10 drops orally, 3 times daily or as otherwise directed by a health care professional. If symptoms persist for more than 7 days, consult your health care professional. Consult a physician for use in children under 12 years of age.

INDICATIONS:

May temporarily relieve soreness after exertion, bruises, strains, sprains, and joint pain and stiffness.**

**Claims based on traditional homeopathic practice, not accepted medical evidence. Not FDA evaluated.

INACTIVE INGREDIENTS:

Demineralized water, 20% Ethanol.

QUESTIONS:

Dist. by Energique, Inc.
201 Apple Blvd.
Woodbine, IA 51579 800.869.8078

PACKAGE LABEL DISPLAY:

ENERGIQUE
SINCE 1987
HOMEOPATHIC REMEDY
TRAUMATONE
1 fl. oz. (30 ml)